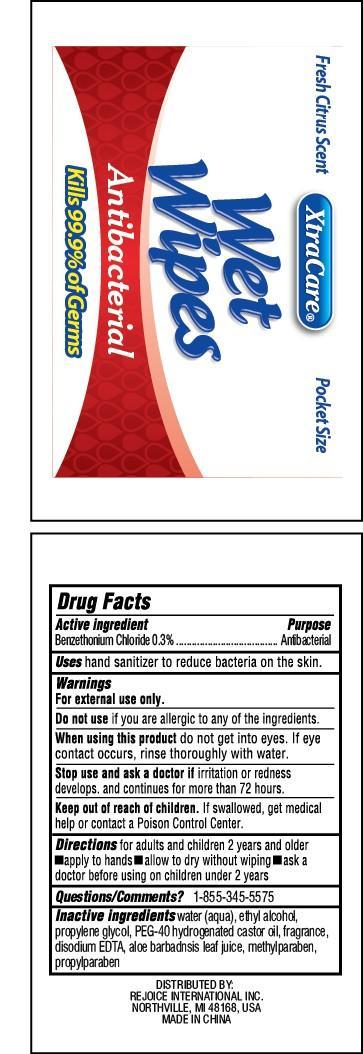 DRUG LABEL: XtraCare Wet Wipes
NDC: 57337-062 | Form: SWAB
Manufacturer: Rejoice International
Category: otc | Type: HUMAN OTC DRUG LABEL
Date: 20250212

ACTIVE INGREDIENTS: BENZETHONIUM CHLORIDE 3 mg/100 mg
INACTIVE INGREDIENTS: WATER; ALCOHOL; PROPYLENE GLYCOL; POLYOXYL 40 HYDROGENATED CASTOR OIL; EDETATE DISODIUM; ALOE VERA LEAF; METHYLPARABEN; PROPYLPARABEN

XtraCare Wet Wipes

Active Ingredient Purpose

Benzethonium Chloride 0.3% .............. Antibacterial

Uses

hand sanitizer to reduce bacteria on the skin.

Keep out of reach of children. If swallowed, get medical help or contact a Poison Control Center

INDICATIONS AND USAGE

XtraCare Wet Wipes

Antibacterial

Fresh Citrus Scent

Pocket Size

Kills 99.9% of Germs

Warnings

For external use only.

Do not use if you are allergic to any of the ingredients.

When using this product do not get into eyes. If eye contact occurs, rinse thoroughly with water.

Stop use and ask a doctor if irritation and redness develops, and continues for more than 72 hours.

Directions

for adults and children 2 years and older

- apply to hands
- allow to dry without wiping
- ask a doctor before using on children under 2 years

Inactive Ingredients

water (aqua), ethyl alcohol, propylene glycol, PEG-40 hydrogenated castor oil, fragrance, disodium EDTA, aloe barbadensis leaf juice, methylparaben, propylparaben

OTHER SAFETY INFORMATION

Questions/comments? 1-855-345-5575

DISTRIBUTED BY

REJOICE INTERNATIONAL INC

NORTHVILLE, MI 48168 USA

MADE IN CHINA